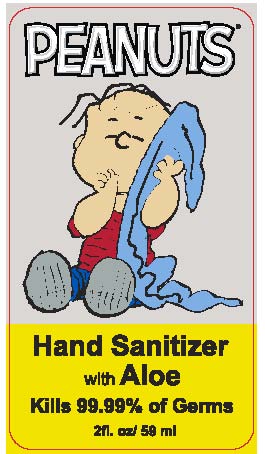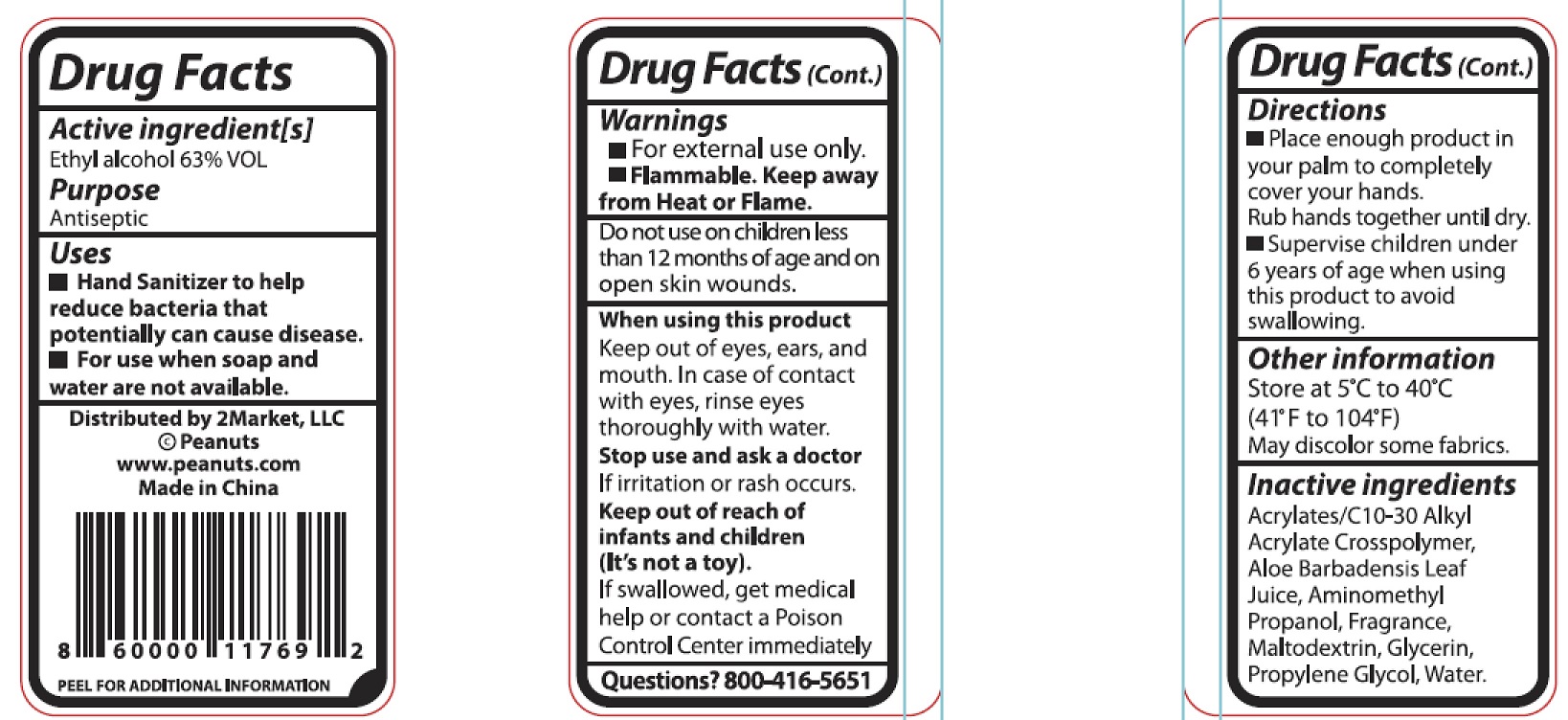 DRUG LABEL: PEANUTS Hand Sanitizer with Aloe
NDC: 76866-002 | Form: GEL
Manufacturer: 2 Market Llc
Category: otc | Type: HUMAN OTC DRUG LABEL
Date: 20200920

ACTIVE INGREDIENTS: ALCOHOL 63 mL/100 mL
INACTIVE INGREDIENTS: MALTODEXTRIN; WATER; CARBOMER COPOLYMER TYPE A (ALLYL PENTAERYTHRITOL CROSSLINKED); ALOE VERA LEAF; AMINOMETHYLPROPANOL; GLYCERIN; PROPYLENE GLYCOL

PEANUTS Hand Sanitizer
with Aloe

Active ingredient[s]

Ethyl alcohol 63% VOL

Purpose

Antiseptic

Uses

- Hand Sanitizer to help reduce bacteria that potentially can cause disease.
- For use when soap and water are not available.

Warnings

- For external use only.
- Flammable. Keep away from Heat or Flame.

Do not use on children less than 12 months of age and on open skin wounds.

When using this product

Keep out of eyes, ears, and mouth. In case of contact with eyes, rinse eyes thoroughly with water.

Stop use and ask a doctor

If irritation or rash occurs.

Keep out of reach of infants and children(It's not a toy).

If swallowed, get medical help or contact a Poison Control Center immediately

Directions

- Place enough product in your palm to completely cover your hands. Rub hands together until dry.
- Supervise children under 6 years of age when using this product to avoid swallowing.

Other information

Store at 5 C to 40 C (41 F to 104 F) May discolor some fabrics.

Inactive ingredients

Acrylates/C10-30 Alkyl Acrylate Crosspolymer, Aloe Barbadensis Leaf Juice, Aminomethyl Propanol, Fragrance, Maltodextrin, Glycerin, Propylene Glycol, Water.